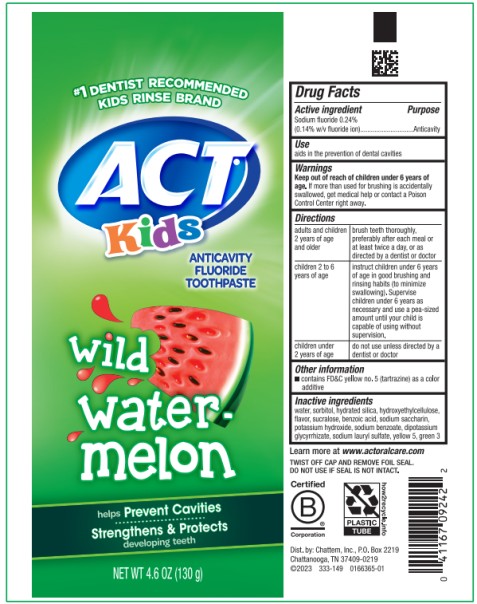 DRUG LABEL: ACT Anticavity Fluoride Kids Wild Watermelon
NDC: 41167-0924 | Form: PASTE
Manufacturer: Chattem, Inc.
Category: otc | Type: HUMAN OTC DRUG LABEL
Date: 20260112

ACTIVE INGREDIENTS: SODIUM FLUORIDE 1.4 mg/1 g
INACTIVE INGREDIENTS: WATER; SORBITOL; HYDRATED SILICA; SUCRALOSE; BENZOIC ACID; SACCHARIN SODIUM; POTASSIUM HYDROXIDE; SODIUM BENZOATE; GLYCYRRHIZINATE DIPOTASSIUM; SODIUM LAURYL SULFATE; FD&C YELLOW NO. 5; FD&C GREEN NO. 3; HYDROXYETHYL CELLULOSE (2000 CPS AT 1%)

ACT Anticavity Fluoride Toothpaste Kids Wild Watermelon

ACT

Kids Anticavity Fluoride Toothpaste

(Wild Watermelon)

Drug Facts

Active ingredient

Sodium fluoride 0.24% (0.14% w/v fluoride ion)

Purpose

Anticavity

Use

■ aids in the prevention of dental cavities

Warnings

Keep out of reach of children under 6 years of age.

If more than used for brushing is accidentally swallowed, get medical help or contact a Poison Control Center right away.

Directions

adults and children 2 years of age and older | brush teeth thoroughly, preferably after each meal or at least twice a day, or as directed by a dentist or doctor
children 2 to 6 years of age | instruct children under 6 years of age in good brushing and rinsing habits (to minimize swallowing). Supervise children under 6 years as necessary and use a pea-sized amount until your child is capable of using without supervision.
children under 2 years of age | do not use unless directed by a dentist or doctor

Other information

■ contains FD&C yellow no. 5 (tartrazine) as a color additive

Inactive ingredients

water, sorbitol, hydrated silica, hydroxyethylcellulose, flavor, sucralose, benzoic acid, sodium saccharin, potassium hydroxide, sodium benzoate, dipotassium glycyrrhizate, sodium lauryl sulfate, yellow 5, green 3

PRINCIPAL DISPLAY PANEL

ACT
Kids
wild
water-
melon
NET WT 4.6 oz (130 g)